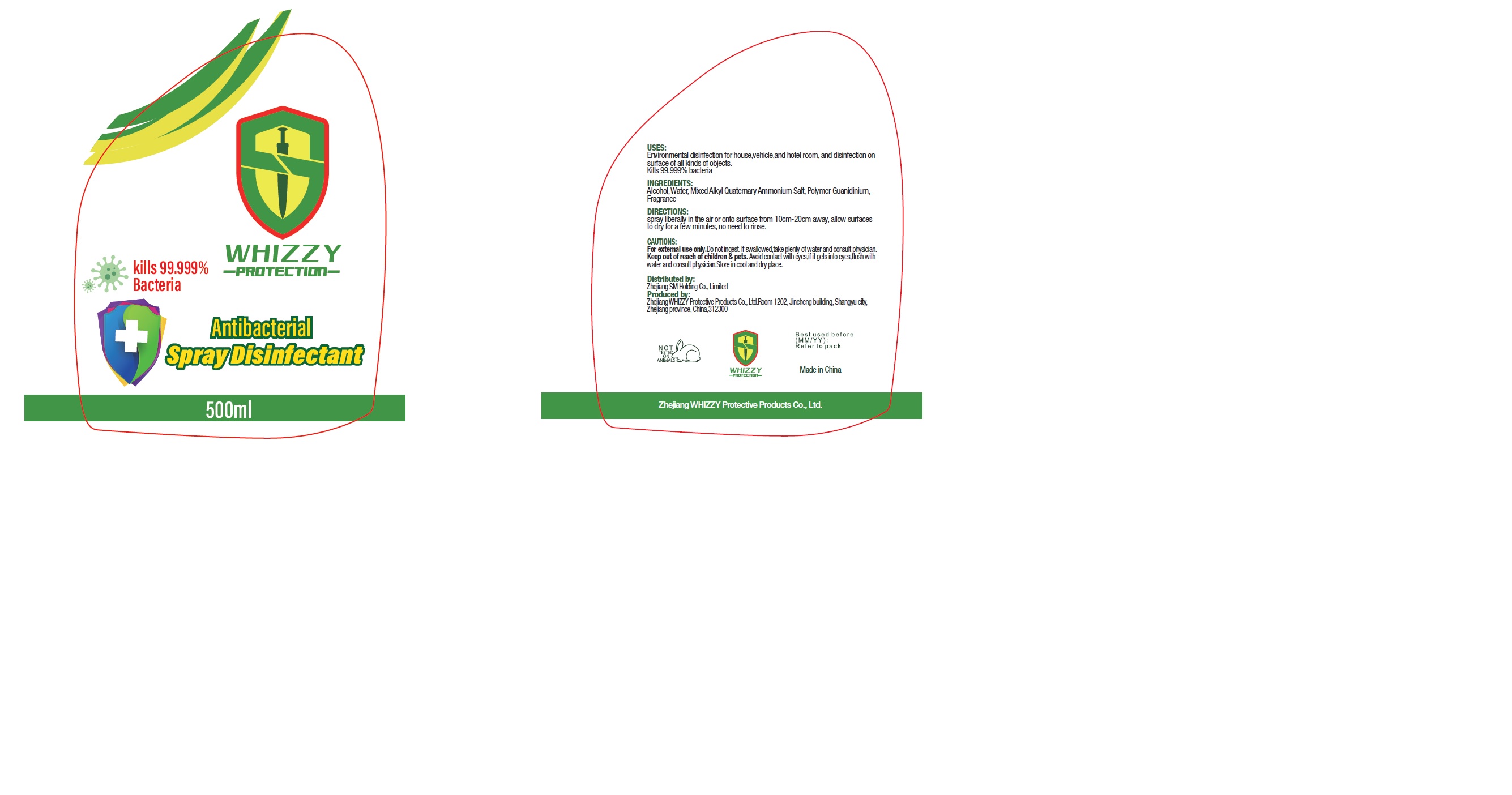 DRUG LABEL: Antibacterial Disinfectant
NDC: 79094-002 | Form: SPRAY
Manufacturer: Zhejiang WHIZZY Protective Products Co.,Ltd
Category: otc | Type: HUMAN OTC DRUG LABEL
Date: 20200917

ACTIVE INGREDIENTS: ALCOHOL 5 mL/100 mL
INACTIVE INGREDIENTS: DIMYRISTYLDIMONIUM CHLORIDE 0.15 mL/100 mL; DILAURYLDIMONIUM CHLORIDE 0.25 mL/100 mL; WATER 94.5 mL/100 mL; LINALOOL, (+/-)- 0.01 mL/100 mL; .ALPHA.-HEXYLCINNAMALDEHYDE 0.01 mL/100 mL; BENZYL ACETATE 0.015 mL/100 mL; LINALYL ACETATE 0.0125 mL/100 mL; METHYL DIHYDROJASMONATE (SYNTHETIC) 0.0125 mL/100 mL; HEXAMETHYLINDANOPYRAN 0.0125 mL/100 mL; BENZYL BENZOATE 0.0125 mL/100 mL; DIPROPYLENE GLYCOL 0.015 mL/100 mL

PURPOSE

Kills 99.999% bacteria

USES

Environmental disinfection for house,vehicle,and hotel room,and disinfection on

surface of all kinds of objects.

Kills 99.999% bacteria

CAUTIONS

For external use only. Do not ingest.If swallowed,take plenty of water and consult physician.

Keep out of reach of children & pets.Avoid contact with eyes,if it gets into eyes,flush with

water and consult physician.Store in cool and dry place

Keep out of reach of children. If swallowed,take plenty of water and consult physician.

Directions

Spary liberally in the air or onto surface from 10cm-20cm away,allow surfaces to dry for a few minutes,no need to rinse

ingredients

Alcohol,Water,Mixed Alkyl Quaternary Ammonium Salt,Polymer Guanidinium,Fragrance

Package Label - Principal Display Panel

500 mL NDC: 79094-002-0101